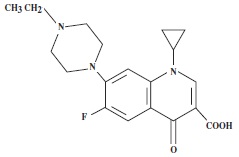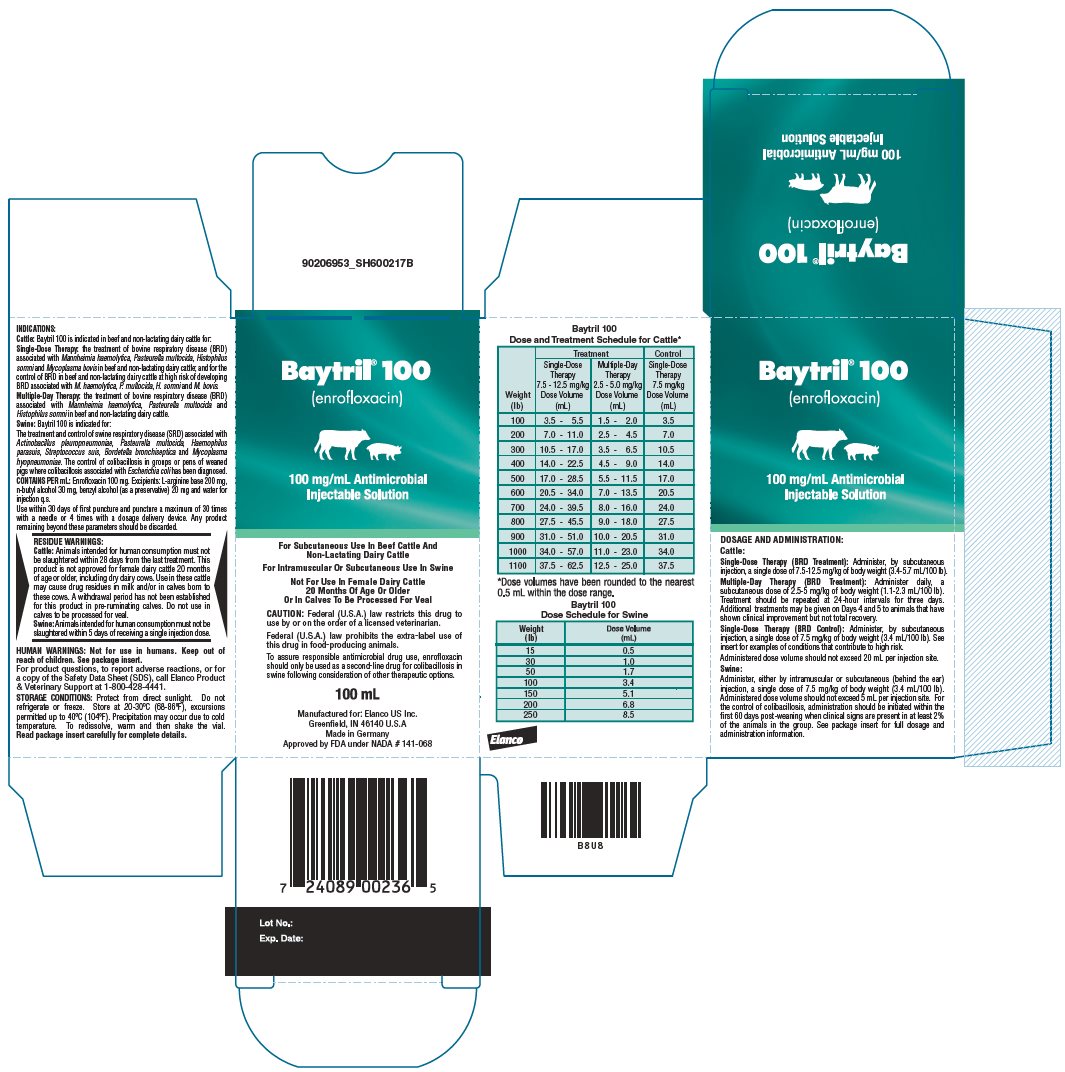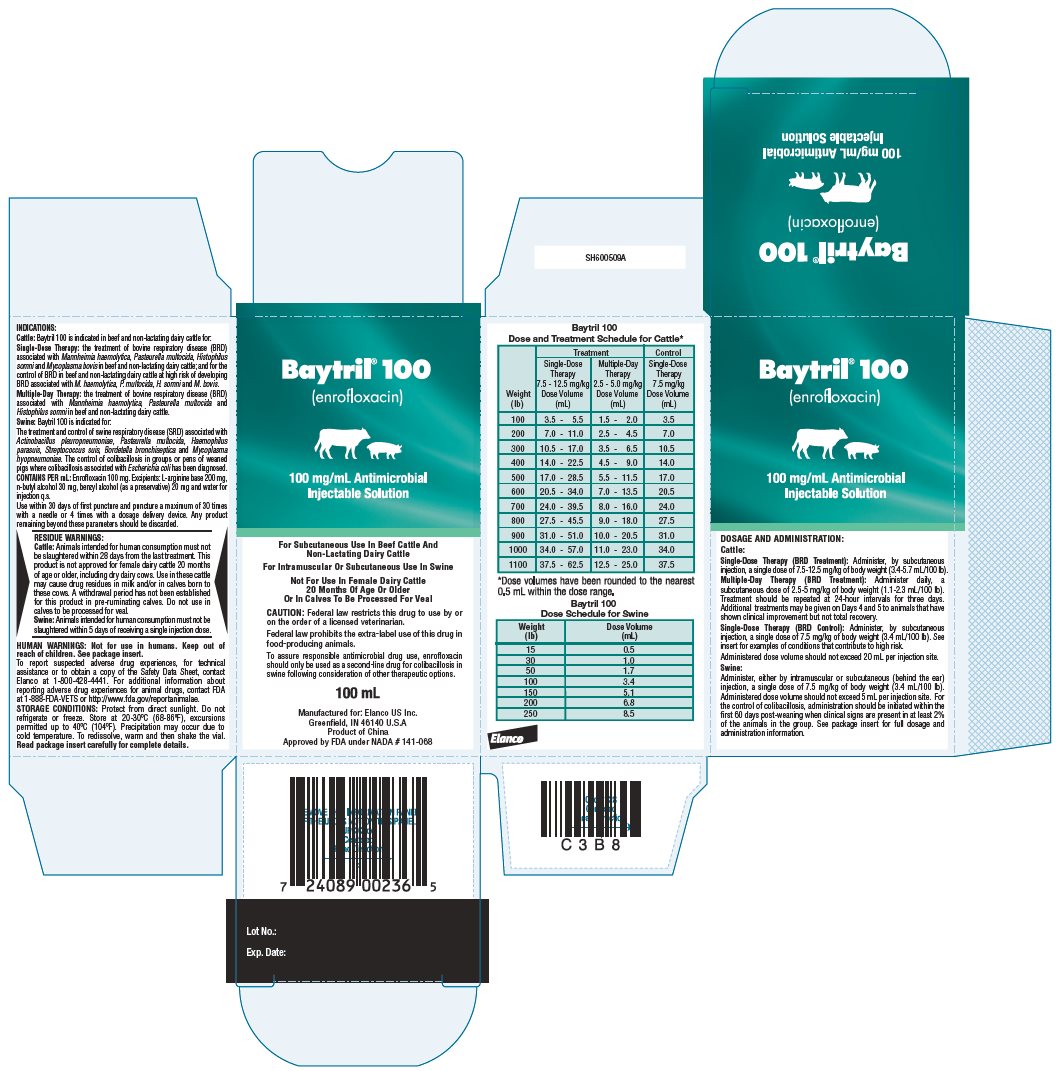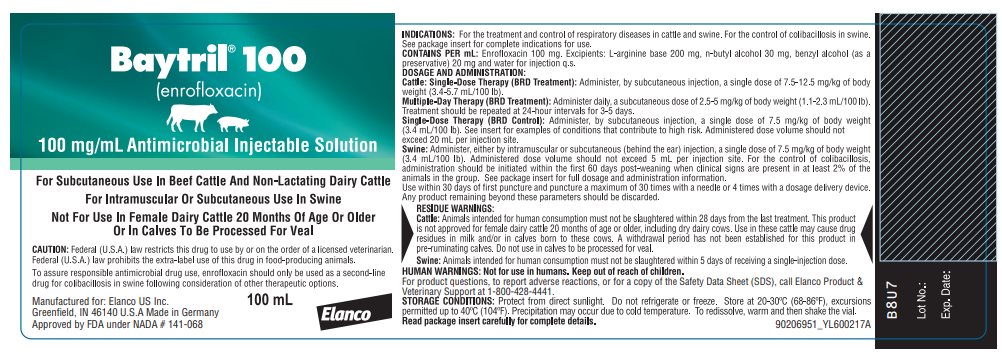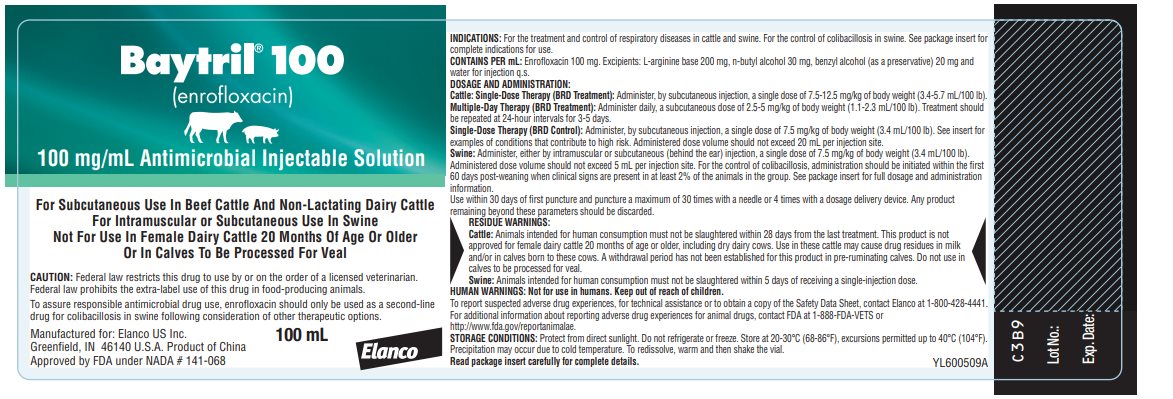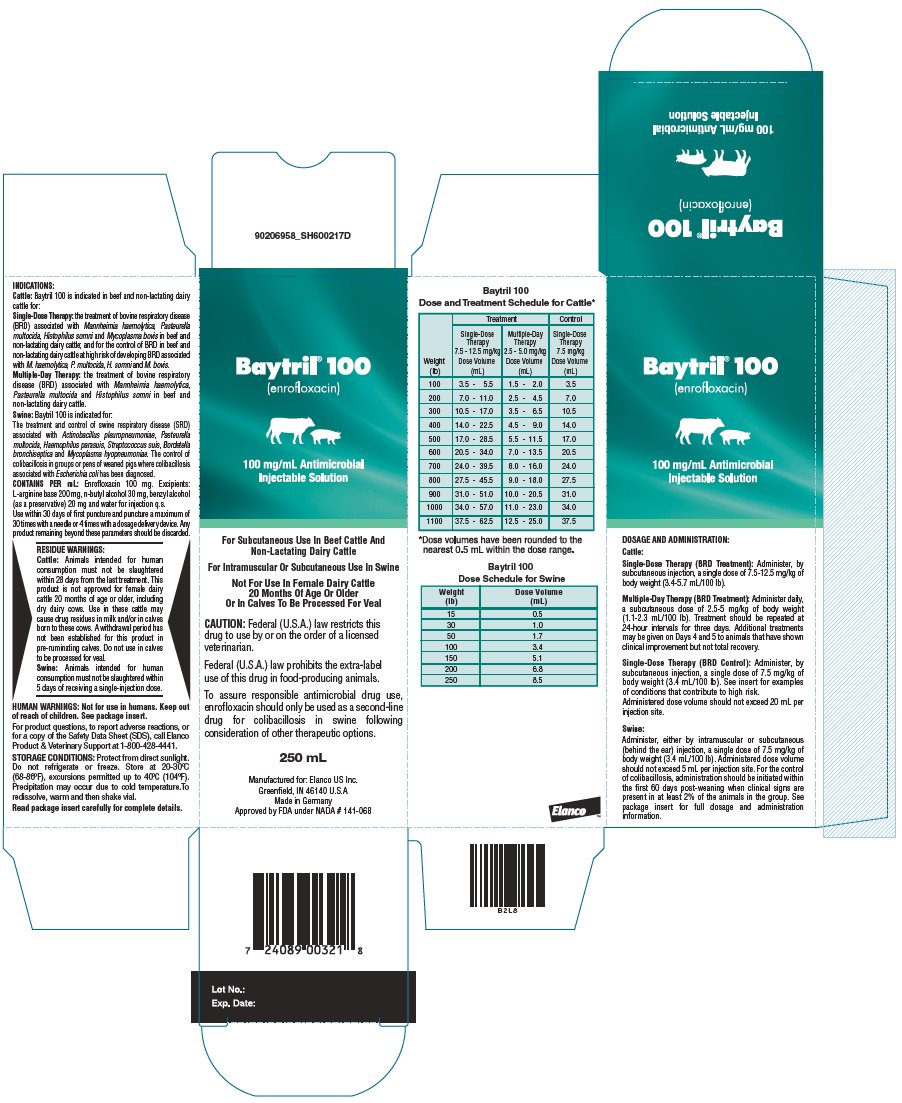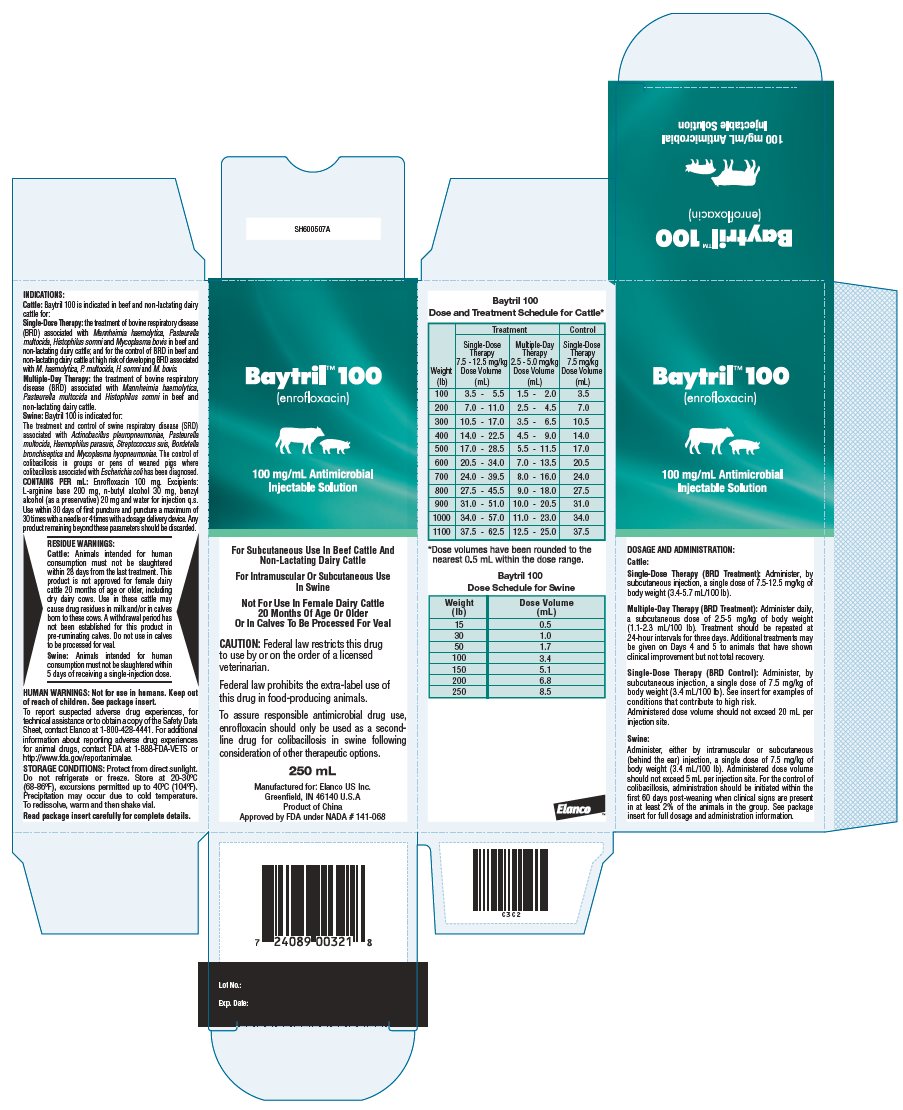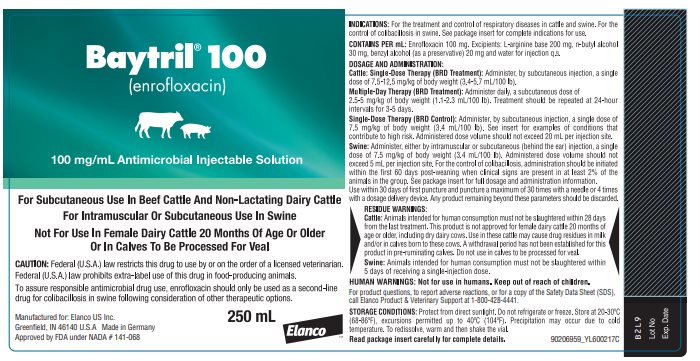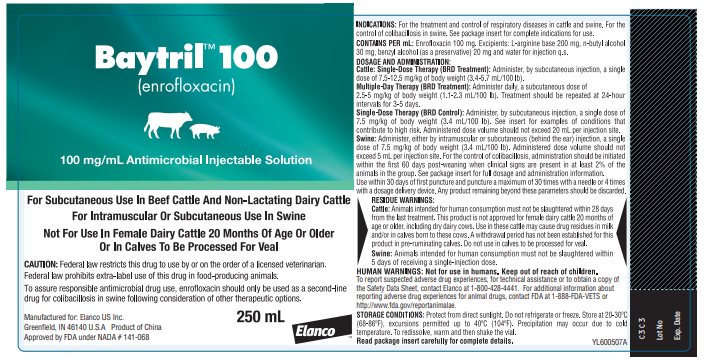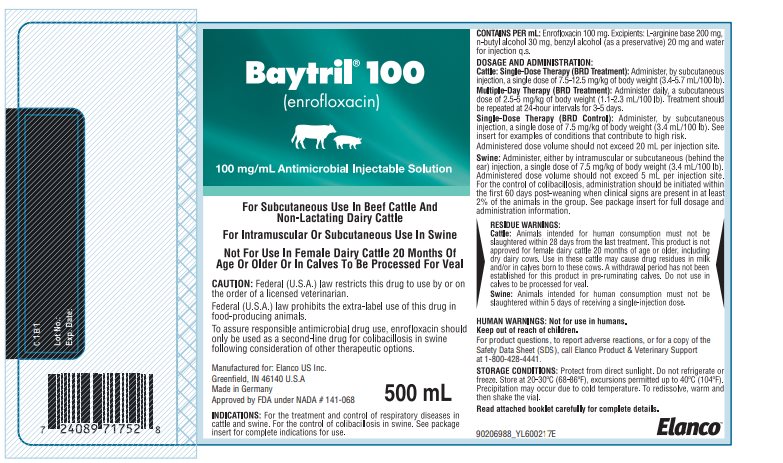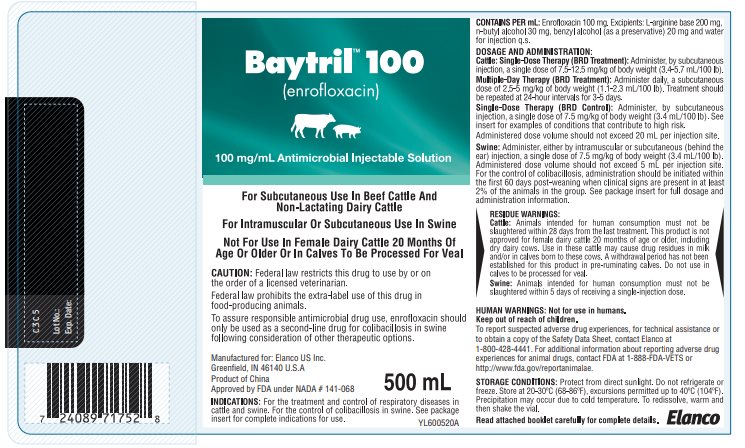 DRUG LABEL: Baytril
NDC: 58198-0021 | Form: INJECTION, SOLUTION
Manufacturer: Elanco US Inc.
Category: animal | Type: PRESCRIPTION ANIMAL DRUG LABEL
Date: 20251001

ACTIVE INGREDIENTS: ENROFLOXACIN 100 mg/1 mL

Elanco™ Baytril® 100

(enrofloxacin)

100 mg/mL Antimicrobial
Injectable Solution

For Subcutaneous Use In Beef Cattle And Non-Lactating Dairy Cattle
For Intramuscular Or Subcutaneous Use In Swine
Not For Use In Female Dairy Cattle 20 Months Of Age Or Older
Or In Calves To Be Processed For Veal

CAUTION:

Federal (U.S.A.) law restricts this drug to use by or on the order of a licensed veterinarian.
Federal law restricts this drug to use by or on the order of a licensed veterinarian.
Federal (U.S.A.) law prohibits the extra-label use of this drug in food-producing animals.
Federal law prohibits the extra-label use of this drug in food-producing animals.

To assure responsible antimicrobial drug use, enrofloxacin should only be used as a second-line drug for colibacillosis in swine following consideration of other therapeutic options.

PRODUCT DESCRIPTION:

Baytril 100 is a sterile, ready-to-use injectable antimicrobial solution that contains enrofloxacin, a broad-spectrum fluoroquinolone antimicrobial agent.

Each mL of Baytril 100 contains 100 mg of enrofloxacin. Excipients are L-arginine base 200 mg, n-butyl alcohol 30 mg, benzyl alcohol (as a preservative) 20 mg and water for injection q.s.

CHEMICAL NOMENCLATURE AND STRUCTURE:

1-cyclopropyl-7-(4-ethyl-1-piperazinyl)-6-fluoro-1,4-dihydro-4-oxo-3-quinolinecarboxylic acid.

INDICATIONS:

Cattle - Single-Dose Therapy: Baytril 100 is indicated for the treatment of bovine respiratory disease (BRD) associated with Mannheimia haemolytica, Pasteurella multocida, Histophilus somni and Mycoplasma bovis in beef and non-lactating dairy cattle; and for the control of BRD in beef and non-lactating dairy cattle at high risk of developing BRD associated with M. haemolytica, P. multocida, H. somni and M. bovis.

Cattle - Multiple-Day Therapy: Baytril 100 is indicated for the treatment of bovine respiratory disease (BRD) associated with Mannheimia haemolytica, Pasteurella multocida and Histophilus somni in beef and non-lactating dairy cattle.

Swine: Baytril 100 is indicated for the treatment and control of swine respiratory disease (SRD) associated with Actinobacillus pleuropneumoniae, Pasteurella multocida, Haemophilus parasuis, Streptococcus suis, Bordetella bronchiseptica and Mycoplasma hyopneumoniae. Baytril 100 is indicated for the control of colibacillosis in groups or pens of weaned pigs where colibacillosis associated with Escherichia coli has been diagnosed.

DOSAGE AND ADMINISTRATION:

Baytril 100 provides flexible dosages and durations of therapy.

Baytril 100 may be administered as a single dose for one day for treatment and control of BRD (cattle), for treatment and control of SRD or for control of colibacillosis (swine), or for multiple days for BRD treatment (cattle). Selection of the appropriate dose and duration of therapy for BRD treatment in cattle should be based on an assessment of the severity of the disease, pathogen susceptibility and clinical response.

Cattle:

Single-Dose Therapy (BRD Treatment): Administer, by subcutaneous injection, a single dose of 7.5-12.5 mg/kg of body weight (3.4-5.7 mL/100 lb).

Multiple-Day Therapy (BRD Treatment): Administer daily, a subcutaneous dose of 2.5-5 mg/kg of body weight (1.1-2.3 mL/100 lb). Treatment should be repeated at 24-hour intervals for three days. Additional treatments may be given on Days 4 and 5 to animals that have shown clinical improvement but not total recovery.

Single-Dose Therapy (BRD Control): Administer, by subcutaneous injection, a single dose of 7.5 mg/kg of body weight (3.4 mL/100 lb).

Examples of conditions that may contribute to calves being at high risk of developing BRD include, but are not limited to, the following:

- Transportation with animals from two or more farm origins.
- An extended transport time with few to no rest stops.
- An environmental temperature change of ≥30°F during transportation.
- A ≥30°F range in temperature fluctuation within a 24-hour period.
- Exposure to wet or cold weather conditions.
- Excessive shrink (more than would be expected with a normal load of cattle).
- Stressful arrival processing procedures (e.g., castration or dehorning).
- Exposure within the prior 72 hours to animals showing clinical signs of BRD.

Administered dose volume should not exceed 20 mL per injection site.

Table 1 – Baytril 100 Dose and Treatment Schedule for Cattle*

Weight (lb) | Treatment |  | Control
Weight (lb) | Single-Dose Therapy 7.5 - 12.5 mg/kg Dose Volume (mL) | Multiple-Day Therapy 2.5 - 5.0 mg/kg Dose Volume (mL) | Single-Dose Therapy 7.5 mg/kg Dose Volume (mL)
100 | 3.5 - 5.5 | 1.5 - 2.0 | 3.5
200 | 7.0 - 11.0 | 2.5 - 4.5 | 7.0
300 | 10.5 - 17.0 | 3.5 - 6.5 | 10.5
400 | 14.0 - 22.5 | 4.5 - 9.0 | 14.0
500 | 17.0 - 28.5 | 5.5 - 11.5 | 17.0
600 | 20.5 - 34.0 | 7.0 - 13.5 | 20.5
700 | 24.0 - 39.5 | 8.0 - 16.0 | 24.0
800 | 27.5 - 45.5 | 9.0 - 18.0 | 27.5
900 | 31.0 - 51.0 | 10.0 - 20.5 | 31.0
1000 | 34.0 - 57.0 | 11.0 - 23.0 | 34.0
1100 | 37.5 - 62.5 | 12.5 - 25.0 | 37.5
*Dose volumes have been rounded to the nearest 0.5 mL within the dose range.

Swine:

Administer, either by intramuscular or subcutaneous (behind the ear) injection, a single dose of 7.5 mg/kg of body weight (3.4 mL/100 lb). Administered dose volume should not exceed 5 mL per injection site.

For the control of colibacillosis, administration should be initiated within the first 60 days post-weaning when clinical signs are present in at least 2% of the animals in the group. If no improvement is noted within 48 hours, the diagnosis should be reevaluated.

Table 2 – Baytril 100 Dose Schedule for Swine

Weight (lb) | Dose Volume (mL)
15 | 0.5
30 | 1.0
50 | 1.7
100 | 3.4
150 | 5.1
200 | 6.8
250 | 8.5

Dilution of Baytril 100: Baytril 100 may be diluted with sterile water prior to injection. The diluted product should be used within 24 hours. Store diluted solution in amber glass bottles between 4-40°C (36-104°F).

Table 3 – Dilution Schedule*

Swine Weight | mL of Baytril 100 | mL of sterile water | Number of doses
10 lb | 34 mL | 66 mL | 100
15 lb | 51 mL | 49 mL | 100
20 lb | 68 mL | 32 mL | 100
25 lb | 85 mL | 15 mL | 100
*For 1 mL dose volume from diluted solution

Use within 30 days of first puncture and puncture a maximum of 30 times with a needle or 4 times with a dosage delivery device. Any product remaining beyond these parameters should be discarded.

RESIDUE WARNINGS:

Cattle: Animals intended for human consumption must not be slaughtered within 28 days from the last treatment. This product is not approved for female dairy cattle 20 months of age or older, including dry dairy cows. Use in these cattle may cause drug residues in milk and/or in calves born to these cows. A withdrawal period has not been established for this product in pre-ruminating calves. Do not use in calves to be processed for veal. Swine: Animals intended for human consumption must not be slaughtered within 5 days of receiving a single-injection dose.

HUMAN WARNINGS:

Not for use in humans. Keep out of reach of children. Avoid contact with eyes. In case of contact, immediately flush eyes with copious amounts of water for 15 minutes. In case of dermal contact, wash skin with soap and water. Consult a physician if irritation persists following ocular or dermal exposures. Individuals with a history of hypersensitivity to quinolones should avoid this product. In humans, there is a risk of user photosensitization within a few hours after excessive exposure to quinolones. If excessive accidental exposure occurs, avoid direct sunlight. For product questions, to report adverse reactions, or for a copy of the Safety Data Sheet (SDS), call Elanco Product & Veterinary Support at 1-800-428-4441.

PRECAUTIONS:

The effects of enrofloxacin on cattle or swine reproductive performance, pregnancy and lactation have not been adequately determined. The long-term effects on articular joint cartilage have not been determined in pigs above market weight.

Subcutaneous injection in cattle and swine, or intramuscular injection in swine, can cause a transient local tissue reaction that may result in trim loss of edible tissue at slaughter.

Baytril 100 contains different excipients than other Baytril products. The safety and efficacy of this formulation in species other than cattle and swine have not been determined.

Quinolone-class drugs should be used with caution in animals with known or suspected Central Nervous System (CNS) disorders. In such animals, quinolones have, in rare instances, been associated with CNS stimulation which may lead to convulsive seizures. Quinolone-class drugs have been shown to produce erosions of cartilage of weight-bearing joints and other signs of arthropathy in immature animals of various species. See Animal Safety section for additional information.

ADVERSE REACTIONS:

No adverse reactions were observed during clinical trials.
To report suspected adverse drug experiences, for technical assistance or to obtain a copy of the Safety Data Sheet, contact Elanco at 1-800-428-4441.

For additional information about reporting adverse drug experiences for animal drugs, contact FDA at 1-888-FDA-VETS or http://www.fda.gov/reportanimalae.

MICROBIOLOGY:

Enrofloxacin is bactericidal and exerts its antibacterial effect by inhibiting bacterial DNA gyrase (a type II topoisomerase) thereby preventing DNA supercoiling and replication which leads to cell death.^1 Enrofloxacin is active against Gram-negative and Gram-positive bacteria.

EFFECTIVENESS:

Cattle: A total of 845 calves with naturally-occurring BRD were treated with Baytril 100 in eight field trials located in five cattle-feeding states. Response to treatment was compared to non-treated controls. Single-dose and multiple-day therapy regimens were evaluated. BRD and mortality were significantly reduced in enrofloxacin-treated calves. No adverse reactions were reported in treated animals.

The effectiveness of Baytril 100 for the control of respiratory disease in cattle at high risk of developing BRD was evaluated in a six-location study in the U.S. and Canada. A total of 1,150 crossbred beef calves at high risk of developing BRD were enrolled in the study. Baytril 100 (7.5 mg/kg BW) or an equivalent volume of sterile saline was administered as a single subcutaneous injection within two days after arrival. Cattle were observed daily for clinical signs of BRD and were evaluated for success on Day 14 post-treatment. Treatment success in the Baytril 100 group (497/573, 87.83%) was significantly higher (P = 0.0013) than success in the saline control group (455/571, 80.92%). In addition, there were more treatment successes (n = 13) than failures (n = 3) in the group of animals positive for M. bovis on Day 0 that were treated with Baytril 100. No product-related adverse reactions were reported.

Swine: A total of 590 pigs were treated with Baytril 100 or saline in two separate natural infection SRD field trials. For the treatment of SRD, the success rate of enrofloxacin-treated pigs that were defined as “sick and febrile” (increased respiratory rate, labored or dyspneic breathing, depressed attitude and a rectal temperature ≥ 104°F) was statistically significantly greater than the success rate of saline-treated “sick and febrile” pigs. For the control of SRD, mean rectal temperature, mortality (one trial) and morbidity were statistically significantly lower for enrofloxacin-treated pigs in pens containing a percentage of “sick and febrile” pigs compared to saline-treated pigs.

The effectiveness of Baytril 100 administered as a single SC dose of 7.5 mg/kg BW for the treatment and control of SRD associated with M. hyopneumoniae was demonstrated using an induced infection model study and three single-site natural infection field studies. In the model study, 72 healthy pigs were challenged with a representative M. hyopneumoniae isolate and treated with Baytril 100 or saline. A statistically significant (P < 0.0001) decrease in the mean total lung lesion score was observed in the Baytril 100-treated group (4%) compared with the saline-treated group (27%) at 10 days post-treatment. In two field studies evaluating effectiveness for treatment of SRD, a total of 300 pigs with clinical signs of SRD (moderate depression, moderately increased respiratory rate, and a rectal temperature of ≥ 104°F) were enrolled and treated with Baytril 100 or saline. At 7 days post-treatment, the cure rate was statistically significantly higher at each site (P < 0.0001) in the Baytril 100-treated groups (61.3% and 92%) compared with the saline-treated groups (26.7% and 33.3%). In one field study evaluating effectiveness for control of SRD, a group of 400 pigs in which > 15% had clinical signs of SRD (moderate depression score, moderately increased respiratory rate, and a rectal temperature of ≥ 104°F) was enrolled and treated with Baytril 100 or saline. At 7 days post-treatment, the cure rate was statistically significantly higher (P < 0.0002) in the Baytril 100-treated group (70.0%) compared with the saline-treated group (48.5%). In addition to M. hyopneumoniae, B. bronchiseptica was also isolated in sufficient numbers from these field studies to be included in the SRD treatment and control indications.

The effectiveness of Baytril 100 for the control of colibacillosis associated with E. coli was evaluated in a multi-site natural infection field study. At each site, when at least 5% of the pigs were defined as “clinically affected” (presence of diarrhea and either depression or gauntness), all pigs were administered Baytril 100 as a single IM dose of 7.5 mg/kg BW or an equivalent dose volume of saline. At 7 days post-treatment, the success rate was statistically significantly higher (P = 0.0350) in the Baytril 100-treated group (61.5%) compared with the saline-treated group (44.7%).

The effectiveness of Baytril 100 administered as a single IM dose of 7.5 mg/kg BW for the treatment and control of SRD or as a single SC dose of 7.5 mg/kg BW for the control of colibacillosis was confirmed by demonstrating comparable serum enrofloxacin concentrations following IM or SC injection into the neck of healthy male and female pigs.

TOXICOLOGY:

The oral LD50 for laboratory rats was greater than 5000 mg/kg of body weight. Ninety-day feeding studies in dogs and rats revealed no observable adverse effects at treatment rates of 3 and 40 mg/kg respectively. Chronic studies in rats and mice revealed no observable adverse effects at 5.3 and 323 mg/kg respectively. There was no evidence of carcinogenic effect in laboratory animal models. A two-generation rat reproduction study revealed no effect with 10 mg/kg treatments. No teratogenic effects were observed in rabbits at doses of 25 mg/kg or in rats at 50 mg/kg.

ANIMAL SAFETY:

Cattle: Safety studies were conducted in feeder calves using single doses of 5, 15 and 25 mg/kg for 15 consecutive days and 50 mg/kg for 5 consecutive days. No clinical signs of toxicity were observed when a dose of 5 mg/kg was administered for 15 days. Clinical signs of depression, incoordination and muscle fasciculation were observed in calves when doses of 15 or 25 mg/kg were administered for 10 to 15 days. Clinical signs of depression, inappetance and incoordination were observed when a dose of 50 mg/kg was administered for 3 days. No drug-related abnormalities in clinical pathology parameters were identified. No articular cartilage lesions were observed after examination of stifle joints from animals administered 25 mg/kg for 15 days.

A safety study was conducted in 23-day-old calves using doses of 5, 15 and 25 mg/kg for 15 consecutive days. No clinical signs of toxicity or changes in clinical pathology parameters were observed. No articular cartilage lesions were observed in the stifle joints at any dose level at 2 days and 9 days following 15 days of drug administration.

An injection site study conducted in feeder calves demonstrated that the formulation may induce a transient reaction in the subcutaneous tissue and underlying muscle. No painful responses to administration were observed.

Swine: Subcutaneous Safety: A safety study was conducted in 32 pigs weighing approximately 57 kg (125 lb) using single doses of 5, 15 or 25 mg/kg daily for 15 consecutive days. Incidental lameness of short duration was observed in all groups, including the saline-treated controls. Musculoskeletal stiffness was observed following the 15 and 25 mg/kg treatments with clinical signs appearing during the second week of treatment. Clinical signs of lameness improved after treatment ceased and most animals were clinically normal at necropsy.

A second study was conducted in two pigs weighing approximately 23 kg (50 lb), treated with 50 mg/kg for 5 consecutive days. There were no clinical signs of toxicity or pathological changes.

An injection site study conducted in pigs demonstrated that the formulation may induce a transient reaction in the subcutaneous tissue. No painful responses to administration were observed.

Intramuscular Safety: A safety study was conducted in 48 weaned, 20- to 22-day-old pigs. Pigs were administered Baytril 100, at 7.5, 22.5 and 37.5 mg/kg BW by IM injection into the neck once weekly for 3 consecutive weeks. All pigs remained clinically normal throughout the study. Transient decreases in feed and water consumption were observed after each treatment. Mild, transient, post-treatment injection site swellings were observed in pigs receiving the 37.5 mg/kg BW dose. Injection site inflammation was found on post-mortem examination in all enrofloxacin-treated groups.

STORAGE CONDITIONS:

Protect from direct sunlight. Do not refrigerate or freeze. Store at 20-30ºC (68-86ºF), excursions permitted up to 40ºC (104ºF). Precipitation may occur due to cold temperature. To redissolve, warm and then shake the vial.

HOW SUPPLIED:

Baytril 100:

100 mg/mL | 100 mL Bottle
100 mg/mL | 250 mL Bottle
100 mg/mL | 500 mL Bottle

REFERENCES:

1. Hooper, D. C., Wolfson, J. S., Quinolone Antimicrobial Agents, 2nd ed, 59 - 75, 1993.

For product questions, to report adverse reactions, or for a copy of the Safety Data Sheet (SDS), call Elanco Product & Veterinary Support at 1-800-428-4441.

Elanco
90206956_PA600217X
Revised: January 2022
Baytril is sold by Elanco or its affiliates and is not a product of Bayer. The product name Baytril is owned by Bayer and used under license.
Elanco and the diagonal bar logo are trademarks of Elanco or its affiliates.
© 2022 Elanco or its affiliates.

Baytril 100
Approved by FDA under NADA # 141-068
Manufactured for: Elanco US Inc.
Greenfield, IN 46140 U.S.A
Made in Germany
PA600507X
Baytril is sold by Elanco or its affiliates and is not a product of Bayer. The product name Baytril is owned by Bayer and used under license.
Elanco and the diagonal bar logo are trademarks of Elanco or its affiliates.
© 2025 Elanco or its affiliates.

Baytril 100
Approved by FDA under NADA # 141-068
Manufactured for: Elanco US Inc.
Greenfield, IN 46140 U.S.A
Product of China

Principal Display Panel – 100 mL Carton Label

Baytril® 100

(enrofloxacin)

100 mg/mL Antimicrobial
Injectable Solution

For Subcutaneous Use In Beef Cattle And
Non-Lactating Dairy Cattle

For Intramuscular Or Subcutaneous Use In Swine

Not For Use In Female Dairy Cattle
20 Months Of Age Or Older
Or In Calves To Be Processed For Veal

CAUTION: Federal (U.S.A.) law restricts this drug to
use by or on the order of a licensed veterinarian.

Federal (U.S.A.) law prohibits the extra-label use of
this drug in food-producing animals.

To assure responsible antimicrobial drug use, enrofloxacin
should only be used as a second-line drug for colibacillosis in
swine following consideration of other therapeutic options.

100 mL

Manufactured for: Elanco US Inc.
Greenfield, IN 46140 U.S.A
Made in Germany
Approved by FDA under NADA # 141-068

Baytril® 100

(enrofloxacin)

100 mg/mL Antimicrobial
Injectable Solution

For Subcutaneous Use In Beef Cattle And
Non-Lactating Dairy Cattle

For Intramuscular Or Subcutaneous Use In Swine

Not For Use In Female Dairy Cattle
20 Months Of Age Or Older
Or In Calves To Be Processed For Veal

CAUTION: Federal law restricts this drug to
use by or on the order of a licensed veterinarian.

Federal (U.S.A.) law prohibits the extra-label use of
this drug in food-producing animals.

To assure responsible antimicrobial drug use, enrofloxacin
should only be used as a second-line drug for colibacillosis in
swine following consideration of other therapeutic options.

100 mL

Manufactured for: Elanco US Inc.
Greenfield, IN 46140 U.S.A
Product of China
Approved by FDA under NADA # 141-068

Principal Display Panel – 100 mL Bottle Label

Baytril® 100

(enrofloxacin)

100 mg/mL Antimicrobial Injectable Solution

For Subcutaneous Use In Beef Cattle And Non-Lactating Dairy Cattle
For Intramuscular Or Subcutaneous Use In Swine
Not For Use In Female Dairy Cattle 20 Months Of Age Or Older
Or In Calves To Be Processed For Veal

CAUTION: Federal (U.S.A.) law restricts this drug to use by or on the order of a licensed veterinarian.
Federal (U.S.A.) law prohibits the extra-label use of this drug in food-producing animals.

To assure responsible antimicrobial drug use, enrofloxacin should only be used as a second-line
drug for colibacillosis in swine following consideration of other therapeutic options.

Manufactured for: Elanco US Inc.
Greenfield, IN 46140 U.S.A Made in Germany
Approved by FDA under NADA # 141-068

100 mL

Elanco

Baytril® 100

(enrofloxacin)

100 mg/mL Antimicrobial Injectable Solution

For Subcutaneous Use In Beef Cattle And Non-Lactating Dairy Cattle
For Intramuscular Or Subcutaneous Use In Swine
Not For Use In Female Dairy Cattle 20 Months Of Age Or Older
Or In Calves To Be Processed For Veal

CAUTION: Federal law restricts this drug to use by or on the order of a licensed veterinarian.
Federal law prohibits the extra-label use of this drug in food-producing animals.

To assure responsible antimicrobial drug use, enrofloxacin should only be used as a second-line
drug for colibacillosis in swine following consideration of other therapeutic options.

Manufactured for: Elanco US Inc.
Greenfield, IN 46140 U.S.A Product of China
Approved by FDA under NADA # 141-068

100 mL

Elanco

Principal Display Panel – 250 mL Carton Label

Baytril® 100

(enrofloxacin)

100 mg/mL Antimicrobial
Injectable Solution

For Subcutaneous Use In Beef Cattle And
Non-Lactating Dairy Cattle

For Intramuscular Or Subcutaneous Use In Swine

Not For Use In Female Dairy Cattle
20 Months Of Age Or Older
Or In Calves To Be Processed For Veal

CAUTION: Federal (U.S.A.) law restricts this
drug to use by or on the order of a licensed
veterinarian.

Federal (U.S.A.) law prohibits the extra-label
use of this drug in food-producing animals.

To assure responsible antimicrobial drug use,
enrofloxacin should only be used as a second-line
drug for colibacillosis in swine following
consideration of other therapeutic options.

250 mL

Manufactured for: Elanco US Inc.
Greenfield, IN 46140 U.S.A
Made in Germany
Approved by FDA under NADA # 141-068

BaytrilTM 100

(enrofloxacin)

100 mg/mL Antimicrobial
Injectable Solution

For Subcutaneous Use In Beef Cattle And
Non-Lactating Dairy Cattle

For Intramuscular Or Subcutaneous Use
In Swine

Not For Use In Female Dairy Cattle
20 Months Of Age Or Older
Or In Calves To Be Processed For Veal

CAUTION: Federal (U.S.A.) law restricts this drug
to use by or on the order of a licensed
veterinarian.

Federal law prohibits the extra-label use of
this drug in food-producing animals.

To assure responsible antimicrobial drug use,
enrofloxacin should only be used as a second-
line drug for colibacillosis in swine following
consideration of other therapeutic options.

250 mL

Manufactured for: Elanco US Inc.
Greenfield, IN 46140 U.S.A
Product of China
Approved by FDA under NADA # 141-068

Principal Display Panel – 250 mL Bottle Label

Baytril® 100

(enrofloxacin)

100 mg/mL Antimicrobial Injectable Solution

For Subcutaneous Use In Beef Cattle And Non-Lactating Dairy Cattle
For Intramuscular Or Subcutaneous Use In Swine
Not For Use In Female Dairy Cattle 20 Months Of Age Or Older
Or In Calves To Be Processed For Veal

CAUTION: Federal (U.S.A.) law restricts this drug to use by or on the order of a licensed veterinarian.
Federal (U.S.A.) law prohibits the extra-label use of this drug in food-producing animals.

To assure responsible antimicrobial drug use, enrofloxacin should only be used as a second-line
drug for colibacillosis in swine following consideration of other therapeutic options.

Manufactured for: Elanco US Inc.
Greenfield, IN 46140 U.S.A Made in Germany
Approved by FDA under NADA # 141-068

250 mL

ElancoTM

Baytril® 100

(enrofloxacin)

100 mg/mL Antimicrobial Injectable Solution

For Subcutaneous Use In Beef Cattle And Non-Lactating Dairy Cattle
For Intramuscular Or Subcutaneous Use In Swine
Not For Use In Female Dairy Cattle 20 Months Of Age Or Older
Or In Calves To Be Processed For Veal

CAUTION: Federal law restricts this drug to use by or on the order of a licensed veterinarian.
Federal law prohibits the extra-label use of this drug in food-producing animals.

To assure responsible antimicrobial drug use, enrofloxacin should only be used as a second-line
drug for colibacillosis in swine following consideration of other therapeutic options.

Manufactured for: Elanco US Inc.
Greenfield, IN 46140 U.S.A Product of China
Approved by FDA under NADA # 141-068

250 mL

ElancoTM

Principal Display Panel – 500 mL Bottle Label

Baytril® 100

(enrofloxacin)

100 mg/mL Antimicrobial Injectable Solution

For Subcutaneous Use In Beef Cattle And
Non-Lactating Dairy Cattle

For Intramuscular Or Subcutaneous Use In Swine

Not For Use In Female Dairy Cattle 20 Months Of
Age Or Older Or In Calves To Be Processed For Veal

CAUTION: Federal (U.S.A.) law restricts this drug to use by or on
the order of a licensed veterinarian.

Federal (U.S.A.) law prohibits the extra-label use of this drug in
food-producing animals.

To assure responsible antimicrobial drug use, enrofloxacin should
only be used as a second-line drug for colibacillosis in swine
following consideration of other therapeutic options.

Manufactured for: Elanco US Inc.
Greenfield, IN 46140 U.S.A
Made in Germany
Approved by FDA under NADA # 141-068

500 mL

INDICATIONS: For the treatment and control of respiratory diseases in
cattle and swine. For the control of colibacillosis in swine. See package
insert for complete indications for use.

BaytrilTM 100

(enrofloxacin)

100 mg/mL Antimicrobial Injectable Solution

For Subcutaneous Use In Beef Cattle And
Non-Lactating Dairy Cattle

For Intramuscular Or Subcutaneous Use In Swine

Not For Use In Female Dairy Cattle 20 Months Of
Age Or Older Or In Calves To Be Processed For Veal

CAUTION: Federal (U.S.A.) law restricts this drug to use by or on
the order of a licensed veterinarian.

Federal (U.S.A.) law prohibits the extra-label use of this drug in
food-producing animals.

To assure responsible antimicrobial drug use, enrofloxacin should
only be used as a second-line drug for colibacillosis in swine
following consideration of other therapeutic options.

Manufactured for: Elanco US Inc.
Greenfield, IN 46140 U.S.A
Made in China
Approved by FDA under NADA # 141-068

500 mL

INDICATIONS: For the treatment and control of respiratory diseases in
cattle and swine. For the control of colibacillosis in swine. See package
insert for complete indications for use.

YL600520A